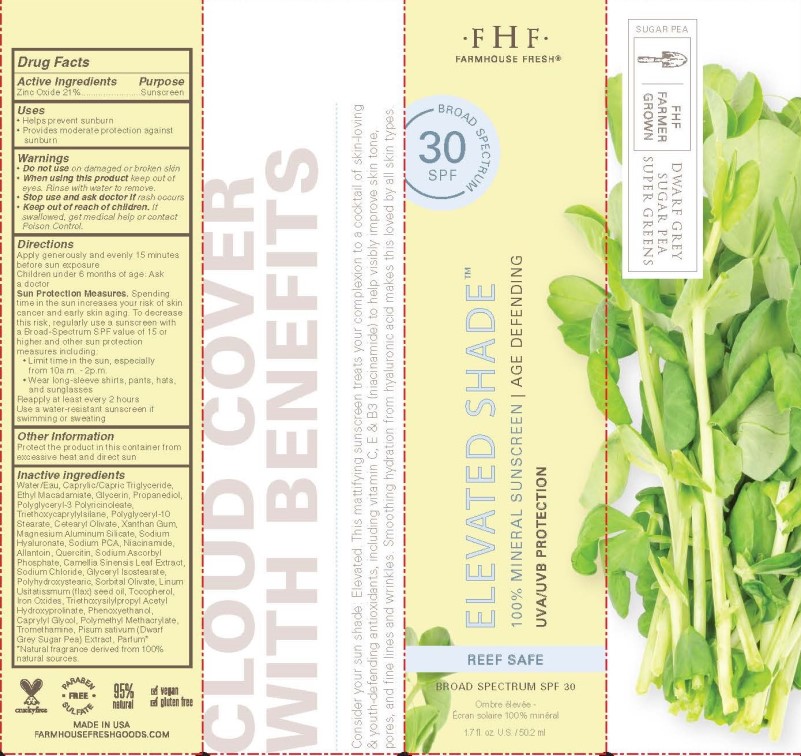 DRUG LABEL: FHF Elevated Shade 100% Mineral Sunscreen
NDC: 59958-601 | Form: LOTION
Manufacturer: Owen Biosciences Inc
Category: otc | Type: HUMAN OTC DRUG LABEL
Date: 20241028

ACTIVE INGREDIENTS: ZINC OXIDE 0.21 g/1 g
INACTIVE INGREDIENTS: WATER

Owen Biosciences FHF Elevated Shade SPF 30

Active Ingredient

Zinc Oxide

Purpose

Sunscreen

Uses

Helps prevent sunburn
Provides moderate protection against sunburn

Warnings

Do not use on broken or damaged skin
When using this product keep out of eyes. Rinse with water to remove.
Stop use and ask docctor if rash occurs
Keep out of reach of children. If swallowed, get medical help or contact Poison Control.

Do not use

on broken or damaged skin

When using this product

keep out of eyes. Rinse with water to remove.

Stop use and ask doctor

if rash occurs

Keep out of reach of children

If swallowed get medical help or contact Poison Control

Directions

Apply generously and evenly 15 minutes before sun exposure
Children under 6 months of age: Ask a doctor
Sun Protection Measures. Spending time in the sun increases your risk of skin cancer and early skin aging. To decreasse this risk, regularly use a sunscreen with a Broad-Spectrum SPF value of 15 or higher and other sun protection measures including
Limit time in the sun especialy from 10a.m. - 2 p.m.
Wear long-sleeve shirts, pants, hats, and sunglasses
Reapply at least every 2 hours
Use a water-resistant sunscreen if swimming or sweating

Other Information

Protect the product in this container from excessive heat and direct sun

Inactive Ingredients

Water, Caprylic/Capric Triglyceride, Ethyl Macadamiate, Glycerin, Propanediol, Polyglyceryl-3 Polyricinoleate, Triethoxycaprylylsilane, Polyglyceryl-10 Stearate, Cetearyl Olivate, Xanthan Gum, Magnesium Aluminum Silicate, Sodium Hyaluronate, Sodium PCA, Niacinamide, Allantoin, Quercitin, Sodium Ascorbyl Phosphate, Camellia Sinensis Leaf Extract, Sodium Chloride, Glyceryl Isostearate, Polyhydroxystearic, Sorbitan Olivate, Linum Usitatissimum (Linseed) Seed Oil, Tocopherol, Iron Oxides, Triethoxysilylpropyl Acetyl Hydroxyprolinate, Phenoxyethanol, Caprylyl Glycol, Polymethyl Methacrylate, Tromethamine, Pisum Sativum (Dwarf Grey Sugar Pea) Extract, Parfum